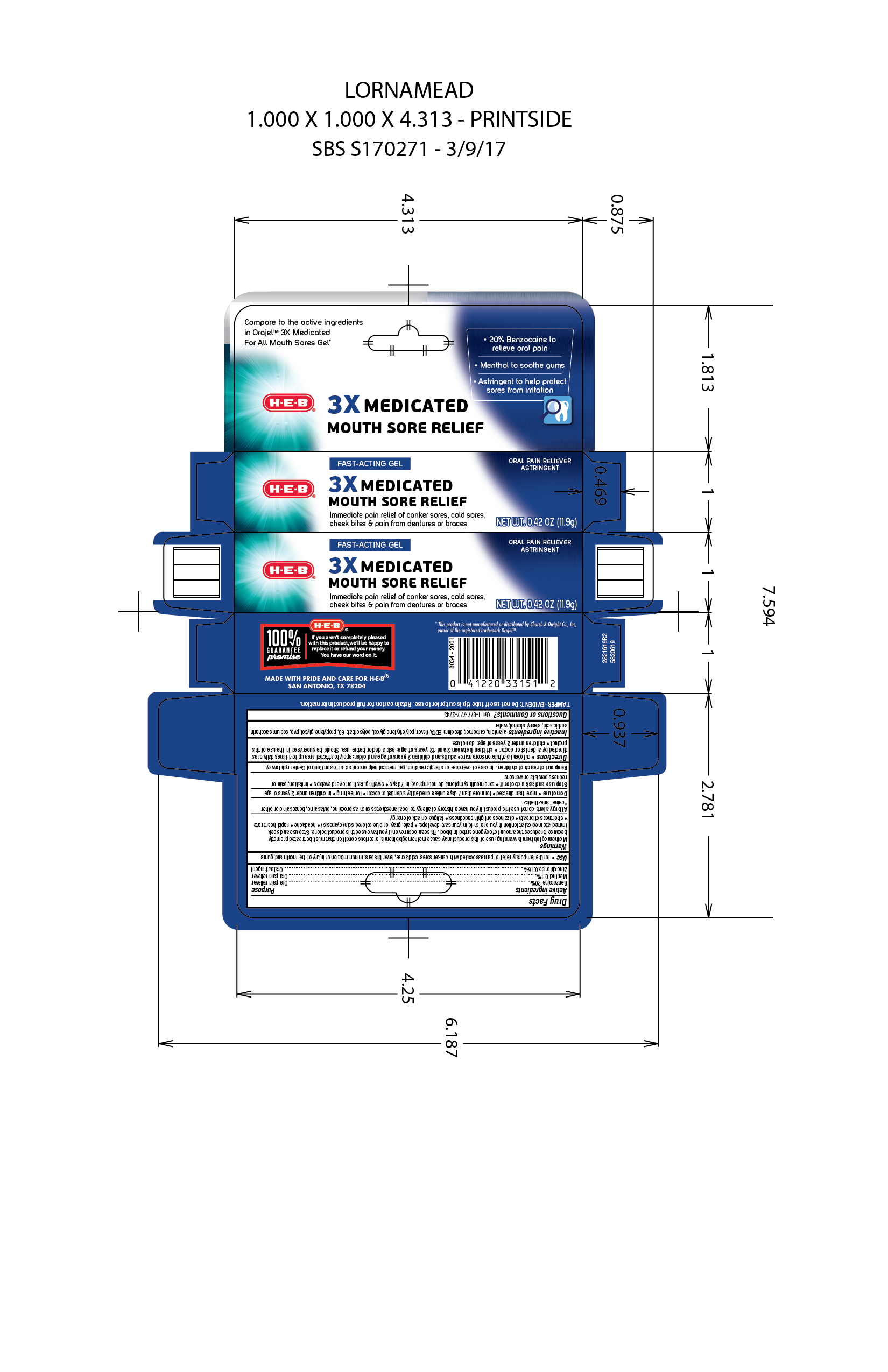 DRUG LABEL: 3x Medicated Mouth Sore Gel
NDC: 37808-691 | Form: GEL
Manufacturer: HEB
Category: otc | Type: HUMAN OTC DRUG LABEL
Date: 20250808

ACTIVE INGREDIENTS: MENTHOL, UNSPECIFIED FORM 0.1 g/100 g; BENZOCAINE 20 g/100 g; ZINC CHLORIDE 0.15 g/100 g
INACTIVE INGREDIENTS: POLYSORBATE 60; POLYETHYLENE GLYCOL 400; PROPYLENE GLYCOL; SACCHARIN SODIUM; METHYL SALICYLATE; POVIDONE K90; STEARYL ALCOHOL; WATER; CARBOMER HOMOPOLYMER TYPE B (ALLYL PENTAERYTHRITOL CROSSLINKED); SORBIC ACID; ALLANTOIN; EDETATE DISODIUM

5820619 Triple Medicated Mouth Sore Gel (8015600)

Active ingredients Purpose

Benzocaine 20% . . . . . .Oral pain reliever

Menthol 0.1% . . . . . . . . Oral pain reliever

Zinc chloride 0.15% . . . .Oral astringent

WARNINGS

Methemoglobinemia warning: use of this product may cause methoglobinemia, a serious condition that must be treated promptly because it reduces the amount of oxygen carried in blood. This can occur even if you have used this product before. Stop use and seek immediate medical attention if you or a child in your care develops: * pale, gray, or blue colored skin (cyanosis) * headache * rapid heart rate * shortness of breath * dizziness or lightheadedness * fatigue or lack of energy

Allergy alert

Allergy alert: do not use this product if you have a history of allergy to local anesthetics such as procaine, butacaine, benzocaine or other "caine" anesthetics

Do not use

- more than directed
- for more than 7 days unless directed by a dentist or doctor
- for teething
- in children under 2 years of age

Stop use and ask a doctor if

- sore mouth symptoms do not improve in 7 days
- swelling, rash or fever develops
- irritaiton, pain or redness persists or worsens

Keep out of reach of children. In case of overdose, get medical help or contact a Poison Control Center right away.

INACTIVE INGREDIENT

allantoin, carbomer, disodium EDTA, flavor, polyethylene glycol, polysorbate 60, propylene glycol, pvp, sodium saccharin, sorbic acid, stearyl alcohol, water

Questions and Comments? Call 1-877-7777-2743

PURPOSE

for the temporary relief of pain associated with canker sores, cold sores, fever blisters, minor irritation or injury of the mouth and gums

Directions

- cut open tip of tube on score mark
- do not use if tip is cut prior to opening
- adults and children 2 years of age and older: apply to affected area up to 4 times daily or as directed by a dentist or doctor.
- Children between 2 and 12 years of age: ask a doctor before use. Should be supervised in the use of this product
- children under 2 years of age: do not use

DOSAGE AND ADMINISTRATION

- cut open tip of tube on score mark
- do not use if tip is cut prior to opening
- adults and children 2 years of age and older: apply to affected area up to 4 times daily or as directed by a dentist or doctor.
- Children between 2 and 12 years of age: ask a doctor before use. Should be supervised in the use of this product
- children under 2 years of age: do not use